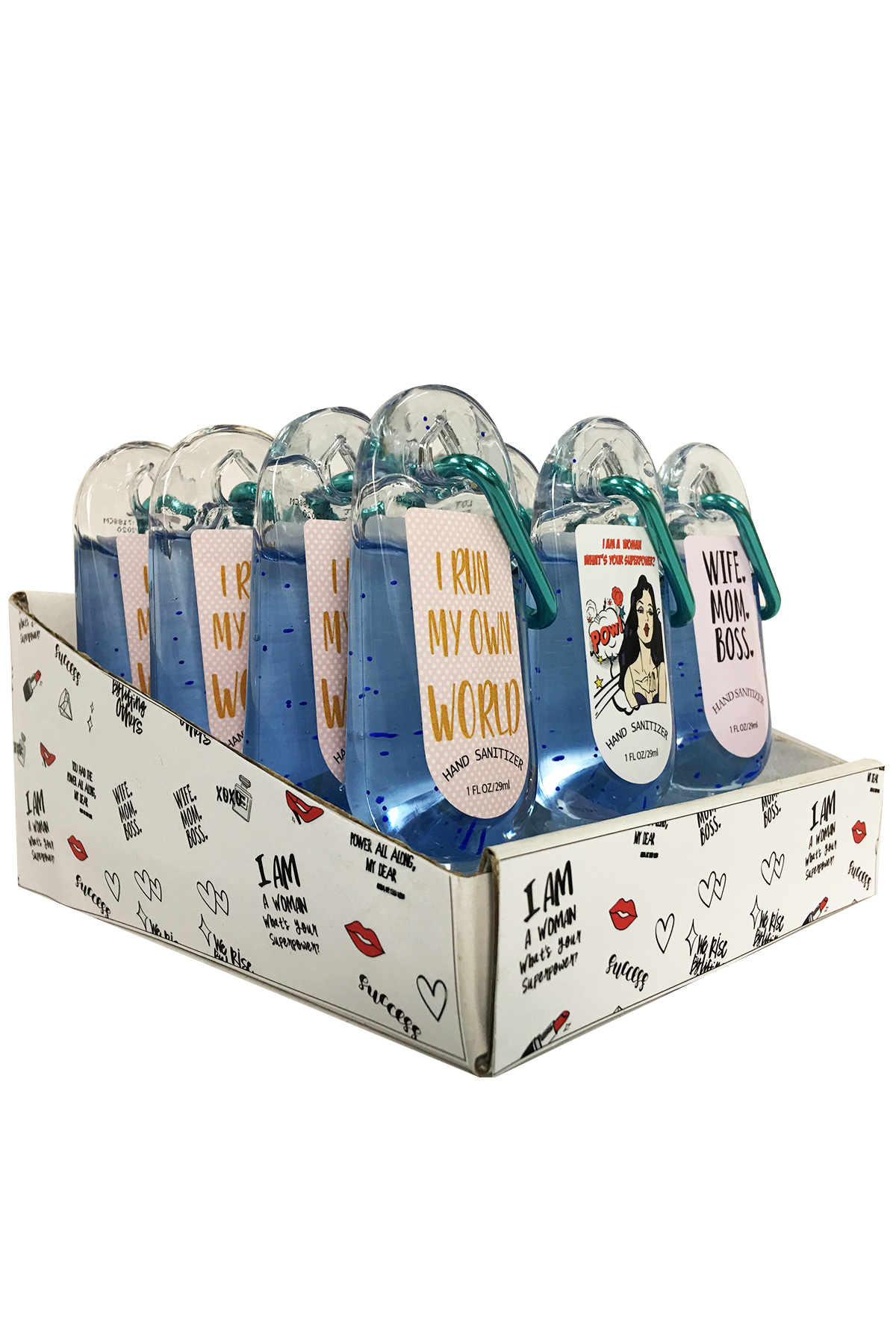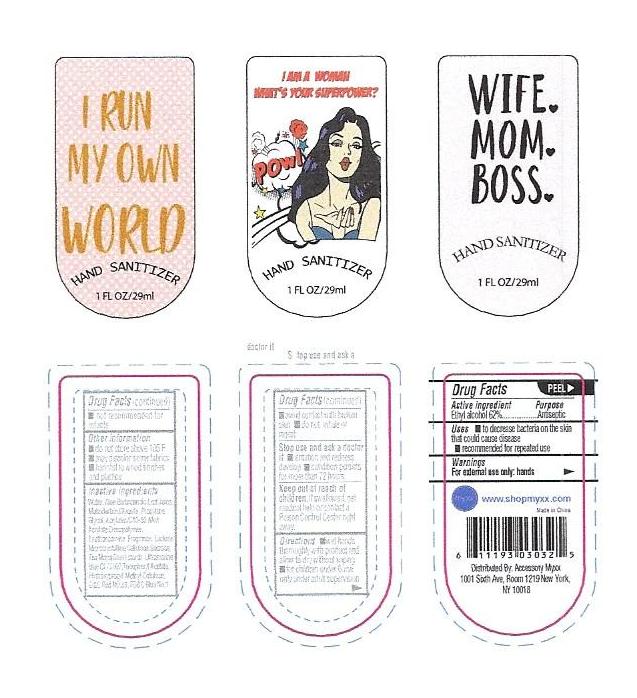 DRUG LABEL: Instant Hand Sanitizer
NDC: 72619-1219 | Form: GEL
Manufacturer: Acessory Myxx LLC
Category: otc | Type: HUMAN OTC DRUG LABEL
Date: 20200413

ACTIVE INGREDIENTS: ALCOHOL 62 mL/100 mL
INACTIVE INGREDIENTS: WATER; MICROCRYSTALLINE CELLULOSE; FD&C BLUE NO. 1; LACTOSE MONOHYDRATE; SUCROSE; ZEA MAYS POLLEN; ULTRAMARINE BLUE; 3-HEXYLOXYPROPYLENE GLYCOL; (C10-C30)ALKYL METHACRYLATE ESTER; GLYCERIN; MALTODEXTRIN; D&C RED NO. 33

Hand Sanitizer

Instant Hand Sanitizer

Warnings
For external use only: hands

Keep out of reach of
children.If swallowed, get
medical help or contact a
Poison Control Center right
away.

Stop use and ask a doctor
if irritation and redness
develop condition persists
for more than 72 hours

aviid contact with broken
skin do not inhale or
ingest

General Warnings

Warnings
For external use only: hands

Keep out of reach of
children.If swallowed, get
medical help or contact a
Poison Control Center right
away.

Stop use and ask a doctor
if irritation and redness
develop condition persists
for more than 72 hours

aviid contact with broken
skin do not inhale or
ingest

ACTIVE INGREDIENT

Ethyl alcohol 62%

INDICATIONS AND USAGE

Use to decrease bacteria on the skin. Use on hands only.

INACTIVE INGREDIENT

Water, Aloe Barbadensis Leaf Juice,
Maltodextrin,Glycerin, Propylene
Glycol, Acrylates/C10-30 Alkyl
Acrylate Crosspolymer,
Triethanoamine, Fragrance, Lactose,
Microcrystalline Cellulose,Sucrose,
Zea Mays(Corn) starch, Ultramarine
blue CI 77007,Tocopheryl Acetate,
Hydroxypropyl Methyl Cellulose,
D&C Red NO.33, FD&C Blue No.1

PURPOSE

To clean hands and fight bacteria on that skin

DOSAGE AND ADMINISTRATION

Squeeze the bottle on your hands so the liquid comes out. Rub hands together. Allow hands to dry.

KEEP OUT OF REACH OF CHILDREN

Not intended for children under the age of 12. Please keep out of reach of children.